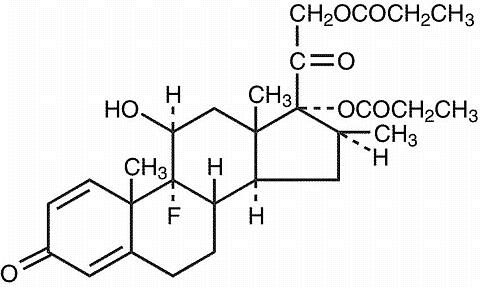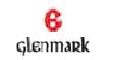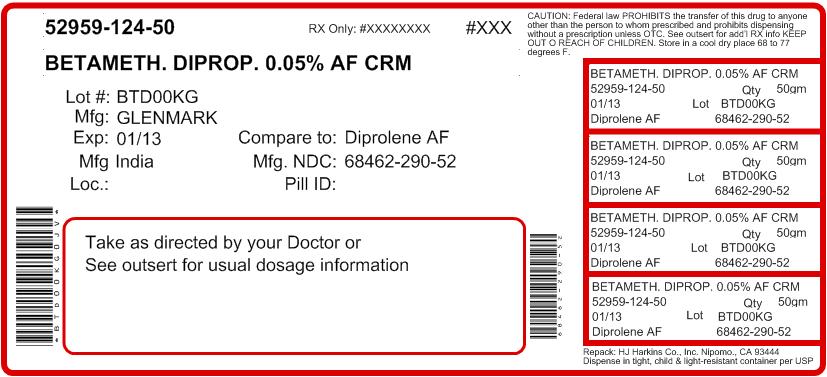 DRUG LABEL: Betamethasone Dipropionate
NDC: 52959-124 | Form: CREAM
Manufacturer: H.J. Harkins Company, Inc.
Category: prescription | Type: HUMAN PRESCRIPTION DRUG LABEL
Date: 20120103

ACTIVE INGREDIENTS: BETAMETHASONE DIPROPIONATE 0.5 mg/1 g
INACTIVE INGREDIENTS: CHLOROCRESOL; PROPYLENE GLYCOL; SODIUM HYDROXIDE; SORBITOL; PETROLATUM; WHITE WAX; CARBOMER HOMOPOLYMER TYPE C; CYCLOMETHICONE; CETEARETH-30

Betamethasone Dipropionate Cream, 0.05% (Augmented*)

(potency expressed as betamethasone)

*Vehicle augments the penetration of the steroid.

For Dermatologic Use Only - Not for Ophthalmic Use

DESCRIPTION

Betamethasone dipropionate cream, 0.05% (augmented) contains betamethasone dipropionate, USP, a synthetic adrenocorticosteroid, for dermatologic use in an emollient base. Betamethasone, an analog of prednisolone, has a high degree of corticosteroid activity and a slight degree of mineralocorticoid activity. Betamethasone dipropionate is the 17, 21-dipropionate ester of betamethasone.

Chemically, betamethasone dipropionate is 9-fluoro-11β,17,21-trihydroxy-16β-methylpregna-1,4-diene-3,20-dione 17,21-dipropionate, with the empirical formula C28H37FO7, a molecular weight of 504.6, and the following structural formula :

Betamethasone dipropionate is a white to creamy white, odorless crystalline powder, insoluble in water.

Each gram of betamethasone dipropionate cream, 0.05% (augmented) contains: 0.643 mg betamethasone dipropionate USP (equivalent to 0.5 mg betamethasone) in an emollient cream base of purified water USP; chlorocresol NF; propylene glycol USP; white petrolatum USP; white wax NF; cyclomethicone NF; sorbitol solution USP; glyceryl oleate/propylene glycol; ceteareth-30; carbomer homopolymer NF; and sodium hydroxide NF.

CLINICAL PHARMACOLOGY

The corticosteroids are a class of compounds comprising steroid hormones secreted by the adrenal cortex and their synthetic analogs. In pharmacologic doses, corticosteroids are used primarily for their anti-inflammatory and/or immunosuppressive effects.

Topical corticosteroids, such as betamethasone dipropionate, are effective in the treatment of corticosteroid-responsive dermatoses primarily because of their anti-inflammatory, antipruritic, and vasoconstrictive actions. However, while the physiologic, pharmacologic, and clinical effects of the corticosteroids are well known, the exact mechanisms of their actions in each disease are uncertain. Betamethasone dipropionate, a corticosteroid, has been shown to have topical (dermatologic) and systemic pharmacologic and metabolic effects characteristic of this class of drugs.

Pharmacokinetics:

The extent of percutaneous absorption of topical corticosteroids is determined by many factors including the vehicle, the integrity of the epidermal barrier, and the use of occlusive dressings. (See DOSAGE AND ADMINISTRATION section.)

Topical corticosteroids can be absorbed through normal intact skin. Inflammation and/or other disease processes in the skin may increase percutaneous absorption. Occlusive dressings substantially increase the percutaneous absorption of topical corticosteroids. (See DOSAGE AND ADMINISTRATION section.)

Once absorbed through the skin, topical corticosteroids enter pharmacokinetic pathways similar to systemically administered corticosteroids. Corticosteroids are bound to plasma proteins in varying degrees, are metabolized primarily in the liver and excreted by the kidneys. Some of the topical corticosteroids and their metabolites are also excreted into the bile.

Betamethasone dipropionate cream, 0.05% (augmented) was applied once daily at 7 grams per day for 1 week to diseased skin, in adult patients with psoriasis or atopic dermatitis, to study its effects on the hypothalamic-pituitary-adrenal (HPA) axis. The results suggested that the drug caused a slight lowering of adrenal corticosteroid secretion, although in no case did plasma cortisol levels go below the lower limit of the normal range.

Sixty-seven pediatric patients ages 1 to 12 years, with atopic dermatitis, were enrolled in an open-label, hypothalamic-pituitary-adrenal (HPA) axis safety study.Betamethasone dipropionate cream, 0.05% (augmented) was applied twice daily for 2 to 3 weeks over a mean body surface area of 58% (range 35% to 95%). In 19 of 60 (32%) evaluable patients, adrenal suppression was indicated by either a ≤ 5 mcg/dL pre-stimulation cortisol, or a cosyntropin post-stimulation cortisol ≤ 8 mcg/dL and/or an increase of < 7 mcg/dL from the baseline cortisol. Studies performed with betamethasone dipropionate cream, 0.05% (augmented) indicate that it is in the high range of potency as compared with other topical corticosteroids.

INDICATIONS AND USAGE

Betamethasone dipropionate cream, 0.05% (augmented) is a high-potency corticosteroid indicated for relief of the inflammatory and pruritic manifestations of corticosteroid-responsive dermatoses in patients 13 years and older.

CONTRAINDICATIONS

Betamethasone dipropionate cream, 0.05% (augmented) is contraindicated in patients who are hypersensitive to betamethasone dipropionate, to other corticosteroids, or to any ingredient in this preparation.

PRECAUTIONS

General

Systemic absorption of topical corticosteroids has produced reversible HPA axis suppression, manifestations of Cushing's syndrome, hyperglycemia, and glucosuria in some patients.

Conditions which augment systemic absorption include the application of the more potent corticosteroids, use over large surface areas, prolonged use, and the addition of occlusive dressings. Use of more than one corticosteroid-containing product at the same time may increase total systemic glucocorticoid exposure. (See DOSAGE AND ADMINISTRATION section.)

Therefore, patients receiving a large dose of a potent topical steroid applied to a large surface area should be evaluated periodically for evidence of HPA axis suppression by using the urinary free cortisol and ACTH stimulation tests. If HPA axis suppression is noted, an attempt should be made to withdraw the drug, to reduce the frequency of application, or to substitute a less potent steroid.

Recovery of HPA axis function is generally prompt and complete upon discontinuation of the drug. In an open-label pediatric study of 60 evaluable patients, of the 19 who showed evidence of suppression 4 patients were tested 2 weeks after discontinuation of betamethasone dipropionate cream, 0.05% (augmented) and 3 of the 4 (75%) had complete recovery of HPA axis function. Infrequently, signs and symptoms of steroid withdrawal may occur, requiring supplemental systemic corticosteroids.

Children may absorb proportionally larger amounts of topical corticosteroids and thus be more susceptible to systemic toxicity. (See PRECAUTIONS: Pediatric Use:.)

If irritation develops, topical corticosteroids should be discontinued and appropriate therapy instituted.

In the presence of dermatological infections, the use of an appropriate antifungal or antibacterial agent should be instituted. If a favorable response does not occur promptly, the corticosteroid should be discontinued until the infection has been adequately controlled.

Information For Patients:

Patients using topical corticosteroids should receive the following information and instructions. This information is intended to aid in the safe and effective use of this medication. It is not a disclosure of all possible adverse or intended effects.

1. This medication is to be used as directed by the physician and should not be used longer than the prescribed time period. It is for external use only. Avoid contact with the eyes.
2. Patients should be advised not to use this medication for any disorder other than that for which it was prescribed.
3. The treated skin area should not be bandaged or otherwise covered or wrapped as to be occlusive. (See DOSAGE AND ADMINISTRATION section.)
4. Patients should report any signs of local adverse reactions.
5. Other corticosteroid-containing products should not be used with betamethasone dipropionate cream, 0.05% (augmented) without first talking to your physician.

Laboratory Tests:

The following tests may be helpful in evaluating HPA axis suppression:

Urinary free cortisol test
ACTH stimulation test

Carcinogenesis, Mutagenesis, and Impairment of Fertility:

Long-term animal studies have not been performed to evaluate the carcinogenic potential of betamethasone dipropionate.

Betamethasone was negative in the bacterial mutagenicity assay (Salmonella typhimurium and Escherichia coli), and in the mammalian cell mutagenicity assay (CHO/HGPRT). It was positive in the in-vitro human lymphocyte chromosome aberration assay, and equivocal in the in-vivo mouse bone marrow micronucleus assay. This pattern of response is similar to that of dexamethasone and hydrocortisone.

Reproductive studies with betamethasone dipropionate carried out in rabbits at doses of 1.0 mg/kg by the intramuscular route and in mice up to 33 mg/kg by the intramuscular route indicated no impairment of fertility except for dose-related increases in fetal resorption rates in both species. These doses are approximately 5- and 38-fold the human dose based on a mg/m^2 comparison, respectively.

Pregnancy:

Teratogenic Effects: Pregnancy Category C:

Corticosteroids are generally teratogenic in laboratory animals when administered systemically at relatively low dosage levels.

Betamethasone dipropionate has been shown to be teratogenic in rabbits when given by the intramuscular route at doses of 0.05 mg/kg.This dose is approximately 0.2-fold the maximum human dose based on a mg/m^2 comparison. The abnormalities observed included umbilical hernias, cephalocele and cleft palates.

Some corticosteroids have been shown to be teratogenic after dermal application in laboratory animals. There are no adequate and well-controlled studies in pregnant women on teratogenic effects from topically applied corticosteroids. Therefore, topical corticosteroids should be used during pregnancy only if the potential benefit justifies the potential risk to the fetus. Drugs of this class should not be used extensively on pregnant patients, in large amounts, or for prolonged periods of time.

Nursing Mothers:

It is not known whether topical administration of corticosteroids can result in sufficient systemic absorption to produce detectable quantities in breast milk. Systemically administered corticosteroids are secreted into breast milk in quantities not likely to have a deleterious effect on the infant. Nevertheless, a decision should be made whether to discontinue nursing or to discontinue the drug, taking into account the importance of the drug to the mother.

Pediatric Use:

Use of betamethasone dipropionate cream, 0.05% (augmented) in pediatric patients 12 years of age and younger is not recommended. (See CLINICAL PHARMACOLOGY and ADVERSE REACTIONS sections.) In an open-label study, 19 of 60 (32%) evaluable pediatric patients (aged 3 months-12 years old) using betamethasone dipropionate cream, 0.05% (augmented) for treatment of atopic dermatitis demonstrated HPA axis suppression. The proportion of patients with adrenal suppression in this study was progressively greater, the younger the age group. (See CLINICAL PHARMACOLOGY: Pharmacokinetics:)

Pediatric patients may demonstrate greater susceptibility to topical corticosteroid-induced HPA axis suppression and Cushing’s syndrome than mature patients because of a larger skin surface area to body weight ratio.The study described above supports this premise, as adrenal suppression in 9-12 year olds, 6-8 year olds, 2-5 year olds, and 3 months-1 year old was 17%, 32%, 38% and 50% respectively.

Hypothalamic-pituitary-adrenal (HPA) axis suppression, Cushing's syndrome, and intracranial hypertension have been reported in children receiving topical corticosteroids. Manifestations of adrenal suppression in children include linear growth retardation, delayed weight gain, low plasma cortisol levels, and absence of response to ACTH stimulation. Manifestations of intracranial hypertension include bulging fontanelles, headaches, and bilateral papilledema. Chronic corticosteroid therapy may interfere with the growth and development of children.

Geriatric Use:

Clinical studies of betamethasone dipropionate cream, 0.05% (augmented) included 104 subjects who were 65 years of age and over and 8 subjects who were 75 years of age and over. No overall differences in safety or effectiveness were observed between these subjects and younger subjects, and other reported clinical experience has not identified differences in responses between the elderly and younger patients. However, greater sensitivity of some older individuals cannot be ruled out.

ADVERSE REACTIONS

The only local adverse reaction reported to be possibly or probably related to treatment with betamethasone dipropionate cream, 0.05% (augmented) during adult controlled clinical studies was stinging. It occurred in 1 patient, 0.4%, of the 242 patients or subjects involved in the studies.

Adverse reactions reported to be possibly or probably related to treatment with betamethasone dipropionate cream, 0.05% (augmented) during a pediatric clinical study include signs of skin atrophy (telangiectasia, bruising, shininess). Skin atrophy occurred in 7 of 67 (10%) patients, involving all age groups from 3 months - 12 years of age.

The following local adverse reactions are reported infrequently when topical corticosteroids are used as recommended. These reactions dermatitis, allergic contact dermatitis, maceration of the skin, secondary infection, skin atrophy, striae, miliaria.

Systemic absorption of topical corticosteroids has produced reversible hypothalamic-pituitary-adrenal (HPA) axis suppression, manifestations of Cushing’s syndrome, hyperglycemia, and glucosuria in some patients.

OVERDOSAGE

Topically applied corticosteroids can be absorbed in sufficient amounts to produce systemic effects. (See PRECAUTIONS.)

DOSAGE AND ADMINISTRATION

Apply a thin film of betamethasone dipropionate cream, 0.05% (augmented) to the affected skin areas once or twice daily. Treatment with betamethasone dipropionate cream, 0.05% (augmented) should be limited to 45 g per week.

Betamethasone dipropionate cream, 0.05% (augmented) is not to be used with occlusive dressings.

HOW SUPPLIED

Betamethasone dipropionate cream, 0.05% (augmented) is supplied in 15 g (NDC 68462-290-17) and 50 g (NDC 68462-290-52); boxes of one.

STORAGE AND HANDLING

Store at 25°C (77°F); excursions permitted to 15 - 30°C (59 - 86°F) [see USP Controlled Room Temperature].

Manufactured:

Glenmark Generics Ltd.
Village: Kishanpura, Baddi Nalagarh Road
District: Solan, Himachal Pradesh - 174101, India

Manufactured for:

Glenmark Generics Inc., USA
Mahwah, NJ 07430

Questions? 1 (888)721-7115
www.glenmarkgenerics.com

February 2011

Repacked by:
H.J. Harkins Company, Inc.
513 Sandydale Drive
Nipomo, CA 93444